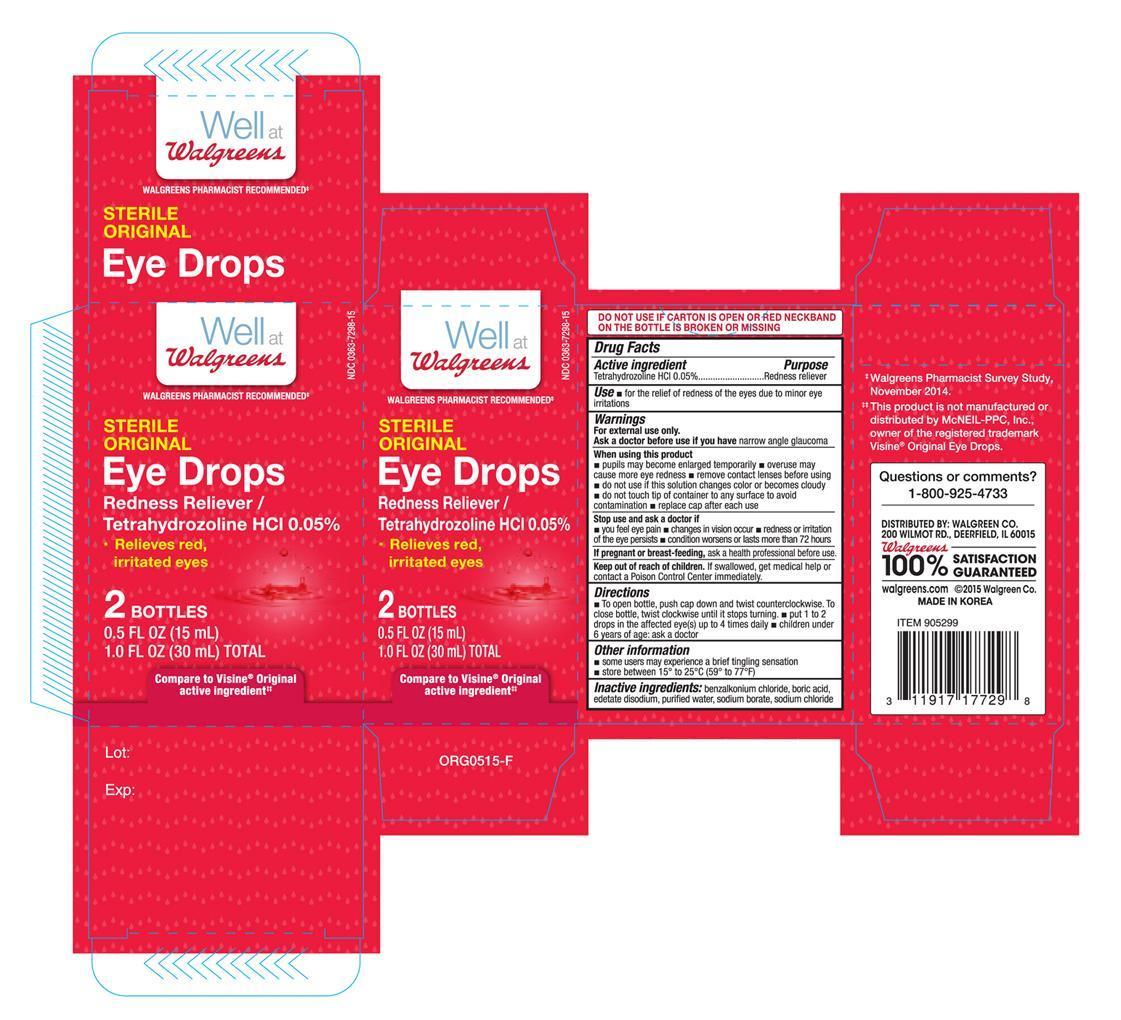 DRUG LABEL: Walgreens Sterile Original Eye
NDC: 0363-7298 | Form: SOLUTION/ DROPS
Manufacturer: Walgreen Company
Category: otc | Type: HUMAN OTC DRUG LABEL
Date: 20150924

ACTIVE INGREDIENTS: TETRAHYDROZOLINE HYDROCHLORIDE 0.5 mg/1 mL
INACTIVE INGREDIENTS: BENZALKONIUM CHLORIDE; BORIC ACID; EDETATE DISODIUM; WATER; SODIUM BORATE; SODIUM CHLORIDE

Active ingredient Purpose

Tetrahydrozoline HCI 0.05............................................... Redness reliever

Use

- for the relief of redness of the eyes due to minor eye irritations

Warnings

For external use only.

Ask a doctor before use if you have narrow angle glaucoma

When using this product

- pupils may become enlarged temporarily
- overuse may cause more eye redness
- remove contact lenses before using
- do not use if this solution changes color or becomes cloudy
- do not touch tip of container to any surface to avoid contamination
- replace cap after each use

Stop use and ask a doctor if

- you feel eye pain
- changes in vision occur
- redness or irritation of the eye persists
- condition worsens or lasts more than 72 hours

PREGNANCY OR BREAST FEEDING

If pregnant or breast-feeding, ask a health professional before use.

Keep out of reach of children. If swallowed, get medical help or contact a Poison Control Center immediately.

Directions

- To open bottle, push cap down and twist counterclockwise. To close bottle, twist clockwise until it stops turning.
- put 1 to 2 drops in the affected eye(s) up to 4 times daily
- children under 6 years of age: ask a doctor

Other information

- some users may experience a brief tingling sensation
- store between 15° to 25°C (59° to 77°F)

INACTIVE INGREDIENT

Inactive ingredients: benzalkonium chloride, boric acid, edetate disodium, purified water, sodium borate, sodium chloride

DOSAGE AND ADMINISTRATION

Distributed by:

Walgreen Co.

200 Wilmot Rd.

Deerfield, IL 60015

Made in Korea